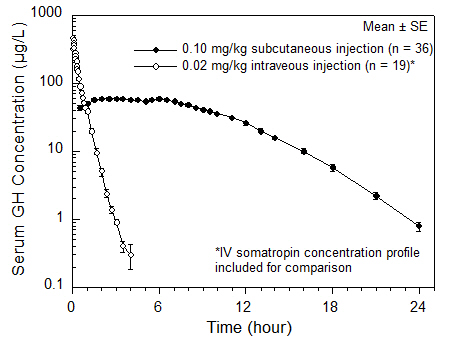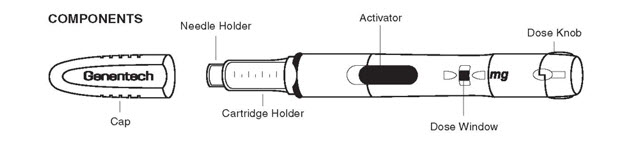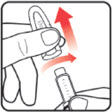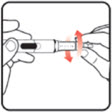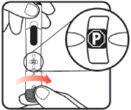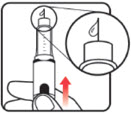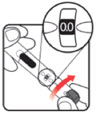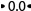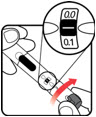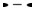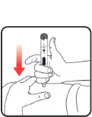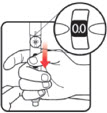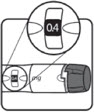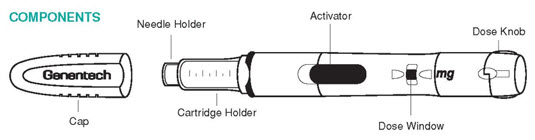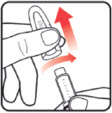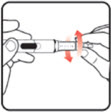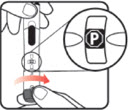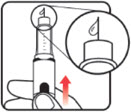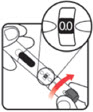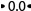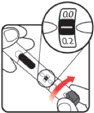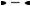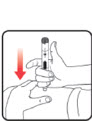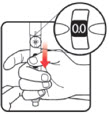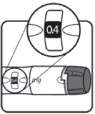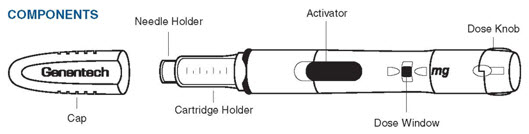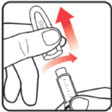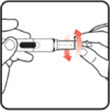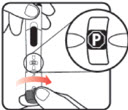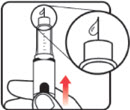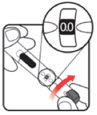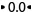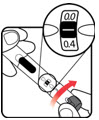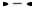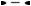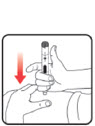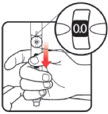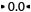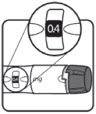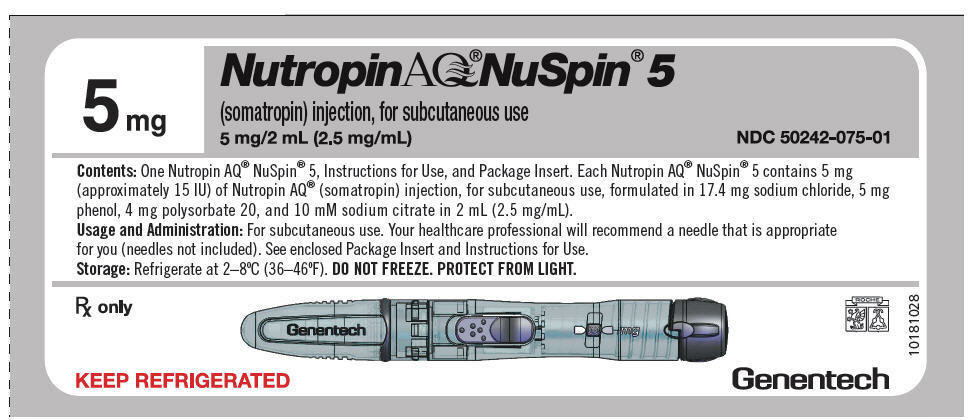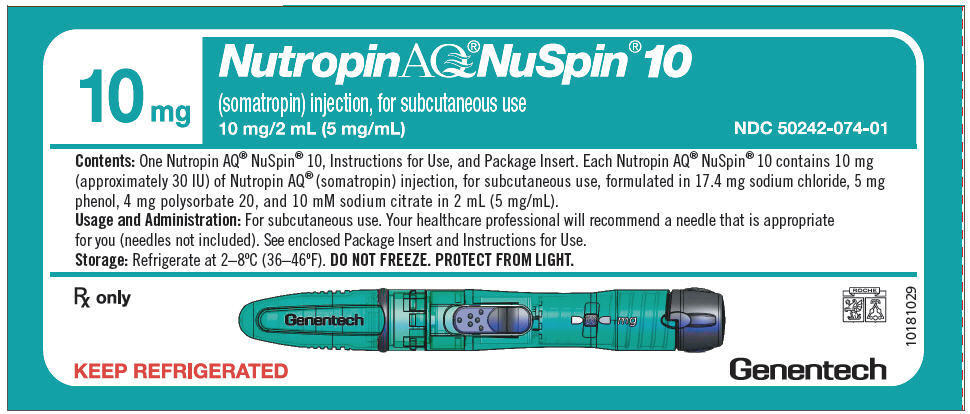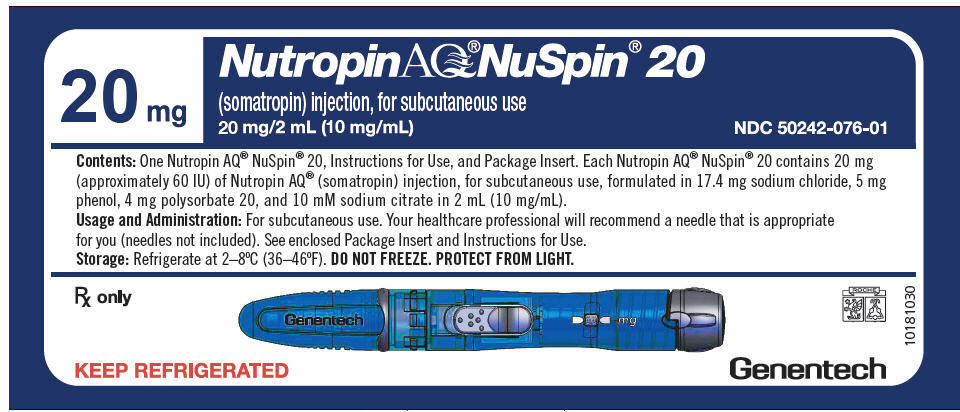 DRUG LABEL: Nutropin AQ NuSpin 5
NDC: 50242-075 | Form: INJECTION, SOLUTION
Manufacturer: Genentech, Inc.
Category: prescription | Type: HUMAN PRESCRIPTION DRUG LABEL
Date: 20250718

ACTIVE INGREDIENTS: SOMATROPIN 5 mg/2 mL
INACTIVE INGREDIENTS: SODIUM CHLORIDE 17.4 mg/2 mL; PHENOL 5 mg/2 mL; POLYSORBATE 20 4 mg/2 mL; SODIUM CITRATE, UNSPECIFIED FORM 10 mmol/2 mL

HIGHLIGHTS OF PRESCRIBING INFORMATION

These highlights do not include all the information needed to use Nutropin AQ safely and effectively. See full prescribing information for Nutropin AQ.
Nutropin AQ (somatropin) injection, for subcutaneous use
Initial U.S. Approval: 1987

RECENT MAJOR CHANGES

Warnings and Precautions, Slipped Capital Femoral Epiphysis in Pediatric Patients (5.10) | 07/2025

1 INDICATIONS AND USAGE

Nutropin AQ is a recombinant human growth hormone indicated for:

- Pediatric Patients: Treatment of children with growth failure due to growth hormone deficiency (GHD), idiopathic short stature (ISS), Turner syndrome (TS), and chronic kidney disease (CKD) up to the time of renal transplantation (1.1).
- Adult Patients: Treatment of adults with either childhood-onset or adult-onset GHD (1.2).

2 DOSAGE AND ADMINISTRATION

Nutropin AQ should be administered subcutaneously (2).

Injection sites should always be rotated to avoid lipoatrophy (2.3).

- Pediatric GHD: | Up to 0.3 mg/kg/week (2.1)
- Pubertal Patients: | Up to 0.7 mg/kg/week (2.1)
- Idiopathic Short Stature: | Up to 0.3 mg/kg/week (2.1)
- Chronic Kidney Disease: | Up to 0.35 mg/kg/week (2.1)
- Turner Syndrome: | Up to 0.375 mg/kg/week (2.1)
- Adult GHD: Either a non-weight based or weight-based dosing regimen may be followed, with doses adjusted based on treatment response and IGF-I concentrations (2.2).
  Non-weight-based: A starting dose of approximately 0.2 mg/day (range 0.15–0.3 mg/day) increased gradually every 1–2 months by increments of approximately 0.1–0.2 mg/day.
  Weight-based: Initiate from not more than 0.006 mg/kg/day; the dose may be increased up to a maximum of 0.025 mg/kg/day in patients ≤ 35 years old or 0.0125 mg/kg/day in patients > 35 years old.

3 DOSAGE FORMS AND STRENGTHS

Nutropin AQ is a sterile liquid available in the following pen cartridge and NuSpin forms (3):

- Pen Cartridge: 10 mg/2 mL (yellow color band), and 20 mg/2 mL (purple color band).
- NuSpin: 5 mg/2 mL (clear device), 10 mg/2 mL (green device), and 20 mg/2 mL (blue device).

4 CONTRAINDICATIONS

- Acute critical illness (4).
- Children with Prader-Willi syndrome (PWS) who are severely obese or have severe respiratory impairment – reports of sudden death (4).
- Active malignancy (4).
- Hypersensitivity to somatropin or excipients (4).
- Active proliferative or severe non-proliferative diabetic retinopathy (4).
- Children with closed epiphysis (4).

5 WARNINGS AND PRECAUTIONS

- Acute critical illness: Evaluate potential benefit of treatment continuation against potential risk (5.1).
- PWS: Evaluate for signs of upper airway obstruction and sleep apnea before initiating therapy. Discontinue treatment if these signs occur. (5.2).
- Neoplasm: Monitor patients with preexisting tumors for progression or reoccurrence. Increased risk of a second neoplasm in childhood cancer survivors treated with somatropin - in particular meningiomas in patients treated with radiation to the head for their first neoplasm. (5.3).
- Impaired glucose tolerance (IGT) and Diabetes Mellitus (DM): Periodically monitor glucose levels in all patients, as IGT and DM may be unmasked during somatropin therapy. Doses of concurrent antihyperglycemic drugs in patients with DM may require adjustment. (5.4).
- Intracranial hypertension (IH): Exclude preexisting papilledema. IH may develop, but is usually reversible after discontinuation or dose reduction (5.5).
- Hypersensitivity: Serious hypersensitivity reactions may occur. In the event of an allergic reaction, seek prompt medical attention (5.6).
- Fluid retention (e.g., edema, arthralgia, carpal tunnel syndrome- especially in adults): Reduce dose as necessary if such signs develop (5.7).
- Hypoadrenalism: Monitor patients for reduced serum cortisol levels and/or need for glucocorticoid dose increase in those with known hypoadrenalism (5.8).
- Hypothyroidism: Monitor thyroid function periodically as it may first become evident or worsen after initiation of somatropin (5.9).
- Slipped capital femoral epiphysis (SCFE): Evaluate any child with onset of a limp or hip/knee pain for possible SCFE and osteonecrosis (5.10).
- Progression of preexisting scoliosis: Monitor any child with scoliosis for progression of the curve (5.11).
- Pancreatitis: Consider pancreatitis in patients with persistent severe abdominal pain (5.16).

6 ADVERSE REACTIONS

Common somatropin-related adverse reactions include injection site reactions. Additional common adverse reactions in adults include edema, arthralgias, and carpal tunnel syndrome (6.1, 6.2).

To report SUSPECTED ADVERSE REACTIONS, contact Genentech at 1-888-835-2555 or FDA at 1-800-FDA-1088 or www.fda.gov/medwatch.

7 DRUG INTERACTIONS

- Inhibition of 11 β-Hydroxysteroid Dehydrogenase Type 1: May require the initiation of glucocorticoid replacement therapy. Patients treated with glucocorticoid replacement for previously diagnosed hypoadrenalism may require an increase in their maintenance doses (7.1, 7.2).
- Glucocorticoid replacement: Should be carefully adjusted (7.2).
- Cytochrome P450- Metabolized Drugs: Monitor carefully if used with somatropin (7.3).
- Oral estrogen: Larger doses of somatropin may be required in women (7.4).
- Insulin and/or other hypoglycemic agents: May require adjustment (7.5).

FULL PRESCRIBING INFORMATION

1 INDICATIONS AND USAGE

1.1 Pediatric Patients

Growth Hormone Deficiency (GHD) - Nutropin AQ® is indicated for the treatment of pediatric patients who have growth failure due to inadequate secretion of endogenous growth hormone (GH).

Growth Failure Secondary to Chronic Kidney Disease (CKD) - Nutropin AQ is indicated for the treatment of growth failure associated with CKD up to the time of renal transplantation. Nutropin AQ therapy should be used in conjunction with optimal management of CKD.

Idiopathic Short Stature (ISS) - Nutropin AQ is indicated for the treatment of ISS, also called non-GHD short stature, defined by height SDS ≤ –2.25, and associated with growth rates unlikely to permit attainment of adult height in the normal range, in pediatric patients whose epiphyses are not closed and for whom diagnostic evaluation excludes other causes associated with short stature that should be observed or treated by other means.

Short Stature Associated with Turner Syndrome (TS) - Nutropin AQ is indicated for the treatment of short stature associated with TS.

1.2 Adult Patients

Nutropin AQ is indicated for the replacement of endogenous GH in adults with GHD who meet either of the following two criteria:

Adult Onset: Patients who have GHD, either alone or associated with multiple hormone deficiencies (hypopituitarism), as a result of pituitary disease, hypothalamic disease, surgery, radiation therapy, or trauma; or

Childhood Onset: Patients who were GH deficient during childhood as a result of congenital, genetic, acquired, or idiopathic causes.

Patients who were treated with somatropin for GHD in childhood and whose epiphyses are closed should be reevaluated before continuation of somatropin therapy at the reduced dose level recommended for GH deficient adults. According to current standards, confirmation of the diagnosis of adult GHD in both groups involves an appropriate GH provocative test with two exceptions: (1) patients with multiple pituitary hormone deficiencies due to organic disease; and (2) patients with congenital/genetic GHD.

2 DOSAGE AND ADMINISTRATION

For subcutaneous injection.

Therapy with Nutropin AQ should be supervised by a physician who is experienced in the diagnosis and management of pediatric patients with short stature associated with growth hormone deficiency (GHD), chronic kidney disease, Turner syndrome, idiopathic short stature, or adult patients with either childhood-onset or adult-onset GHD.

2.1 Dosing for Pediatric Patients

Nutropin AQ dosage and administration schedule should be individualized for each patient. Response to growth hormone (GH) therapy in pediatric patients tends to decrease with time. However, in pediatric patients failure to increase growth rate, particularly during the first year of therapy, suggests the need for close assessment of compliance and evaluation of other causes of growth failure, such as hypothyroidism, under-nutrition, advanced bone age and antibodies to recombinant human GH (rhGH).

Treatment with Nutropin AQ for short stature should be discontinued when the epiphyses are fused.

Pediatric Growth Hormone Deficiency (GHD)

A weekly dosage of up to 0.3 mg/kg of body weight divided into daily subcutaneous injection is recommended.

In pubertal patients, a weekly dosage of up to 0.7 mg/kg divided daily may be used.

Growth Failure Secondary to Chronic Kidney Disease (CKD)

A weekly dosage of up to 0.35 mg/kg of body weight divided into daily subcutaneous injection is recommended.

Nutropin AQ therapy may be continued up to the time of renal transplantation.

In order to optimize therapy for patients who require dialysis, the following guidelines for injection schedule are recommended:

- Hemodialysis patients should receive their injection at night just prior to going to sleep or at least 3 to 4 hours after their hemodialysis to prevent hematoma formation due to the heparin.
- Chronic Cycling Peritoneal Dialysis (CCPD) patients should receive their injection in the morning after they have completed dialysis.
- Chronic Ambulatory Peritoneal Dialysis (CAPD) patients should receive their injection in the evening at the time of the overnight exchange.

Idiopathic Short Stature (ISS)

A weekly dosage of up to 0.3 mg/kg of body weight divided into daily subcutaneous injections is recommended.

Short Stature Associated with Turner Syndrome (TS)

A weekly dosage of up to 0.375 mg/kg of body weight divided into equal doses 3 to 7 times per week by subcutaneous injection is recommended.

2.2 Dosing for Adult Patients

Adult Growth Hormone Deficiency (GHD)

Either of two approaches to Nutropin AQ dosing may be followed: a weight-based regimen or a non-weight-based regimen.

Weight based – Based on the dosing regimen used in the original adult GHD registration trials, the recommended dosage at the start of treatment is not more than 0.006 mg/kg daily. The dose may be increased according to individual patient requirements to a maximum of 0.025 mg/kg daily in patients ≤ 35 years and to a maximum of 0.0125 mg/kg daily in patients over 35 years old. Clinical response, side effects, and determination of age- and gender-adjusted serum insulin-like growth factor (IGF-1) concentrations should be used as guidance in dose titration.

Non-weight based – Alternatively, taking into account the published literature, a starting dose of approximately 0.2 mg/day (range, 0.15 to 0.30 mg/day) may be used without consideration of body weight. This dose can be increased gradually every 1 to 2 months by increments of approximately 0.1 to 0.2 mg/day, according to individual patient requirements based on the clinical response and serum IGF-1 concentrations. The dose should be decreased as necessary on the basis of adverse events and/or serum IGF-1 concentrations above the age- and gender-specific normal range.

Maintenance dosages vary considerably from person to person, and between male and female patients.

A lower starting dose and smaller dose increments should be considered for older patients, who are more prone to the adverse effects of somatropin than younger individuals. In addition, obese individuals are more likely to manifest adverse effects, when treated with a weight-based regimen. In order to reach the defined treatment goal, estrogen-replete women may need higher doses than men. Oral estrogen administration may increase the dose requirements in women.

2.3 Preparation and Administration

The solution should be clear immediately after removal from the refrigerator. Occasionally, after refrigeration, you may notice that small colorless particles of protein are present in the solution. This is not unusual for solutions containing proteins. Allow the pen cartridge or NuSpin® to come to room temperature and gently swirl. If the solution is cloudy, the contents MUST NOT be injected.

Parenteral drug products should always be inspected visually for particulate matter and discoloration prior to administration, whenever solution and container permit.

Injection sites, which may be located on the thigh, upper arm, abdomen or buttock, should always be rotated to avoid lipoatrophy.

Nutropin AQ Pen Cartridge

The Nutropin AQ Pen 10 and 20 mg Cartridges are color-banded to help ensure appropriate use with the Nutropin AQ Pen delivery device. Each cartridge must be used with its corresponding color-coded Nutropin AQ Pen [See Dosage Forms and Strengths (3)].

Wipe the septum of the Nutropin AQ Pen Cartridge with rubbing alcohol or an antiseptic solution to prevent contamination of the contents by microorganisms that may be introduced by repeated needle insertions. It is recommended that Nutropin AQ be administered using sterile, disposable needles. Follow the directions provided in the Nutropin AQ Pen Instructions for Use.

The Nutropin AQ Pen 10 allows for administration of a minimum dose of 0.1 mg to a maximum dose of 4.0 mg, in 0.1 mg increments.

The Nutropin AQ Pen 20 allows for administration of a minimum dose of 0.2 mg to a maximum dose of 8.0 mg, in 0.2 mg increments.

Nutropin AQ NuSpin

The Nutropin AQ NuSpin 5, 10 and 20 are multi-dose, dial-a-dose injection devices prefilled with Nutropin AQ in a 5 mg/2 mL, 10 mg/2 mL or 20 mg/2 mL cartridge, respectively, for subcutaneous use. It is recommended that Nutropin AQ be administered using sterile, disposable needles. Follow the directions provided in the Nutropin AQ NuSpin 5, 10 or 20 Instructions for Use.

The Nutropin AQ NuSpin 5 allows for administration of a minimum dose of 0.05 mg to a maximum dose of 1.75 mg, in increments of 0.05 mg.

The Nutropin AQ NuSpin 10 allows for administration of a minimum dose of 0.1 mg to a maximum dose of 3.5 mg, in increments of 0.1 mg.

The Nutropin AQ NuSpin 20 allows for administration of a minimum dose of 0.2 mg to a maximum dose of 7.0 mg, in increments of 0.2 mg.

3 DOSAGE FORMS AND STRENGTHS

Nutropin AQ is available in the following pen cartridge and NuSpin forms:

- Pen Cartridge: 10 mg/2 mL (yellow color band), and 20 mg/2 mL (purple color band)
- NuSpin: 5 mg/2 mL (clear device), 10 mg/2 mL (green device), and 20 mg/2 mL (blue device)

4 CONTRAINDICATIONS

- Acute Critical Illness

Treatment with pharmacologic amounts of somatropin is contraindicated in patients with acute critical illness due to complications following open heart surgery, abdominal surgery or multiple accidental trauma, or those with acute respiratory failure [see Warnings and Precautions (5.1)].

- Prader-Willi Syndrome (PWS) in Children

Somatropin is contraindicated in patients with PWS who are severely obese, have a history of upper airway obstruction or sleep apnea, or have severe respiratory impairment. There have been reports of sudden death when somatropin was used in such patients. Nutropin AQ is not indicated for the treatment of pediatric patients who have growth failure due to genetically confirmed PWS [see Warnings and Precautions (5.2)].

- Active Malignancy

In general, somatropin is contraindicated in the presence of active malignancy. Any pre-existing malignancy should be inactive and its treatment complete prior to instituting therapy with somatropin. Somatropin should be discontinued if there is evidence of recurrent activity. Since growth hormone deficiency (GHD) may be an early sign of the presence of a pituitary tumor (or, rarely, other brain tumors), the presence of such tumors should be ruled out prior to initiation of treatment. Somatropin should not be used in patients with any evidence of progression or recurrence of an underlying intracranial tumor [see Warnings and Precautions (5.3)].

- Hypersensitivity

Nutropin AQ is contraindicated in patients with a known hypersensitivity to somatropin or any of its excipients. Systemic hypersensitivity reactions have been reported with postmarketing use of somatropin products [see Warnings and Precautions (5.6)].

- Diabetic Retinopathy

Somatropin is contraindicated in patients with active proliferative or severe non-proliferative diabetic retinopathy.

- Closed Epiphysis

Somatropin should not be used for growth promotion in pediatric patients with closed epiphysis.

5 WARNINGS AND PRECAUTIONS

5.1 Acute Critical Illness

Increased mortality in patients with acute critical illnesses due to complications following open heart surgery, abdominal surgery or multiple accidental trauma, or those with acute respiratory failure has been reported after treatment with pharmacologic amounts of somatropin [see Contraindications (4)]. Two placebo-controlled clinical trials in non-GHD adult patients (n = 522) with these conditions in intensive care units revealed a significant increase in mortality (42% vs. 19%) among somatropin-treated patients (doses 5.3–8 mg/day) compared to those receiving placebo. The safety of continuing somatropin treatment in patients receiving replacement doses for approved indications who concurrently develop these illnesses has not been established. Therefore, the potential benefit of treatment continuation with somatropin in patients having acute critical illnesses should be weighed against the potential risk.

5.2 Prader-Willi Syndrome (PWS) in Children

There have been reports of fatalities after initiating therapy with somatropin in pediatric patients with PWS who had one or more of the following risk factors: severe obesity, history of upper airway obstruction or sleep apnea, or unidentified respiratory infection. Male patients with one or more of these factors may be at greater risk than females. Patients with PWS syndrome should be evaluated for signs of upper airway obstruction and sleep apnea before initiation of treatment with somatropin. If during treatment with somatropin, patients show signs of upper airway obstruction (including onset of or increased snoring) and/or new onset sleep apnea, treatment should be interrupted. All patients with PWS treated with somatropin should also have effective weight control and be monitored for signs of respiratory infection, which should be diagnosed as early as possible and treated aggressively [see Contraindications (4)]. Nutropin AQ is not indicated for the treatment of pediatric patients who have growth failure due to genetically confirmed PWS.

5.3 Neoplasms

In childhood cancer survivors who were treated with radiation to the brain/head for their first neoplasm and who developed subsequent GHD and were treated with somatropin, an increased risk of a second neoplasm has been reported. Intracranial tumors, in particular meningiomas, were the most common of these second neoplasms. In adults, it is unknown whether there is any relationship between somatropin replacement therapy and CNS tumor recurrence [see Contraindications (4)]. Monitor all patients with a history of GHD secondary to an intracranial neoplasm routinely while on somatropin therapy for progression or recurrence of the tumor.

Because children with certain rare genetic causes of short stature have an increased risk of developing malignancies, practitioners should thoroughly consider the risks and benefits of starting somatropin in these patients. If treatment with somatropin is initiated, these patients should be carefully monitored for development of neoplasms.

Monitor patients on somatropin therapy carefully for increased growth, or potential malignant changes, of preexisting nevi.

5.4 Glucose Intolerance and Diabetes Mellitus

Treatment with somatropin may decrease insulin sensitivity, particularly at higher doses in susceptible patients. As a result, previously undiagnosed impaired glucose tolerance (IGT) and overt diabetes mellitus may be unmasked during somatropin treatment, and new onset type 2 diabetes mellitus has been reported in patients taking somatropin. Therefore, glucose levels should be monitored periodically in all patients treated with somatropin, especially in those with risk factors for diabetes, such as obesity, Turner syndrome (TS), or a family history of diabetes mellitus. Patients with preexisting type 1 or type 2 diabetes mellitus or IGT should be monitored closely during somatropin therapy. The doses of antihyperglycemic drugs (i.e. insulin or oral/injectable agents) may require adjustment when somatropin therapy is instituted in these patients.

5.5 Intracranial Hypertension

Intracranial Hypertension (IH) with papilledema, visual changes, headache, nausea, and/or vomiting has been reported in a small number of patients treated with somatropin products. Symptoms usually occurred within the first eight (8) weeks after the initiation of somatropin therapy. In all reported cases, IH-associated signs and symptoms rapidly resolved after cessation of therapy or a reduction of the somatropin dose. Funduscopic examination should be performed routinely before initiating treatment with somatropin to exclude preexisting papilledema, and periodically during the course of somatropin therapy. If papilledema is observed by funduscopy during somatropin treatment, treatment should be stopped. If somatropin-induced IH is diagnosed, treatment with somatropin can be restarted at a lower dose after IH-associated signs and symptoms have resolved. Patients with TS, chronic kidney disease (CKD), and PWS may be at increased risk for the development of IH.

5.6 Severe Hypersensitivity

Serious systemic hypersensitivity reactions including anaphylactic reaction and angioedema have been reported with postmarketing use of somatropin products. Patients and caregivers should be informed that such reactions are possible and that prompt medical attention should be sought if an allergic reaction occurs.

5.7 Fluid Retention

Fluid retention during somatropin replacement therapy in adults may occur. Clinical manifestations of fluid retention (e.g., edema, arthralgia, myalgia, nerve compression syndromes including carpal tunnel syndrome/paraesthesias) are usually transient and dose dependent.

5.8 Hypoadrenalism

Patients receiving somatropin therapy who have or are at risk for pituitary hormone deficiency(s) may be at risk for reduced serum cortisol levels and/or unmasking of central (secondary) hypoadrenalism. In addition, patients treated with glucocorticoid replacement for previously diagnosed hypoadrenalism may require an increase in their maintenance or stress doses following initiation of somatropin treatment [see Section 7.1, 11-β Hydroxysteroid Dehydrogenase Type 1].

5.9 Hypothyroidism

Undiagnosed/untreated hypothyroidism may prevent an optimal response to somatropin, in particular, the growth response in children. Patients with TS have an inherently increased risk of developing autoimmune thyroid disease and primary hypothyroidism. In patients with GHD, central (secondary) hypothyroidism may first become evident or worsen during somatropin treatment. Therefore, patients treated with somatropin should have periodic thyroid function tests and thyroid hormone replacement therapy should be initiated or appropriately adjusted when indicated.

5.10 Slipped Capital Femoral Epiphysis (SCFE) in Pediatric Patients

SCFE may occur more frequently in patients with endocrine disorders (including GHD and TS) or in patients undergoing rapid growth. SCFE may lead to osteonecrosis. Cases of SCFE with or without osteonecrosis have been reported in pediatric patients with short stature receiving somatropin, including NUTROPIN AQ. Any pediatric patient with the onset of a limp or complaints of hip or knee pain during NUTROPIN AQ therapy should be evaluated for SCFE and osteonecrosis and managed accordingly.

5.11 Progression of Preexisting Scoliosis in Pediatric Patients

Progression of scoliosis can occur in patients who experience rapid growth. Because somatropin increases growth rate, patients with a history of scoliosis who are treated with somatropin should be monitored for progression of scoliosis. However, somatropin has not been shown to increase the occurrence of scoliosis. Skeletal abnormalities including scoliosis are commonly seen in untreated TS patients. Scoliosis is also commonly seen in untreated patients with PWS. Physicians should be alert to these abnormalities, which may manifest during somatropin therapy.

5.12 Otitis Media and Cardiovascular Disorders in Patients with Turner Syndrome

Patients with TS should be evaluated carefully for otitis media and other ear disorders, as these patients have an increased risk of ear and hearing disorders. Somatropin treatment may increase the occurrence of otitis media in patients with TS. In addition, patients with TS should be monitored closely for cardiovascular disorders (e.g., hypertension, aortic aneurysm or dissection, stroke) as these patients are also at increased risk for these conditions.

5.13 Osteodystrophy in Pediatric Patients with Chronic Kidney Disease

Children with growth failure secondary to CKD should be examined periodically for evidence of progression of renal osteodystrophy. SCFE or avascular necrosis of the femoral head may be seen in children with advanced renal osteodystrophy, and it is uncertain whether these problems are affected by somatropin therapy. X-rays of the hip should be obtained prior to initiating somatropin therapy in CKD patients and physicians and parents should be alert to the development of a limp or complaints of hip or knee pain in these patients treated with Nutropin AQ. No studies have been completed evaluating Nutropin AQ therapy in patients who have received renal transplants. Currently, treatment of patients with functioning renal allografts is not indicated.

5.14 Lipoatrophy

When somatropin is administered subcutaneously at the same site over a long period of time, tissue atrophy may result. This can be avoided by rotating the injection site [see Dosage and Administration (2.3)].

5.15 Laboratory Tests

Serum levels of inorganic phosphorus, alkaline phosphatase, and parathyroid hormone (PTH), and IGF-1 may increase during somatropin therapy.

5.16 Pancreatitis

Cases of pancreatitis have been reported rarely in children and adults receiving somatropin treatment, with some evidence supporting a greater risk in children compared with adults. Published literature indicates that girls who have TS may be at greater risk than other somatropin-treated children. Pancreatitis should be considered in any somatropin–treated patient, especially a child, who develops persistent severe abdominal pain.

6 ADVERSE REACTIONS

The following important adverse reactions are also described elsewhere in the labeling:

- Increased mortality in patients with acute critical illness [see Warnings and Precautions (5.1)]
- Fatalities in children with Prader-Willi syndrome [see Warnings and Precautions (5.2)]
- Neoplasms in pediatric patients [see Warnings and Precautions (5.3)]
- Glucose intolerance and diabetes mellitus [see Warnings and Precautions (5.4)]
- Intracranial hypertension [see Warnings and Precautions (5.5)]
- Severe hypersensitivity [see Warnings and Precautions (5.6)]
- Fluid retention [see Warnings and Precautions (5.7)]
- Hypoadrenalism [see Warnings and Precautions (5.8)]
- Hypothyroidism [see Warnings and Precautions (5.9)]
- Slipped capital femoral epiphysis in pediatric patients [see Warnings and Precautions (5.10)]
- Progression of preexisting scoliosis in pediatric patients [see Warnings and Precautions (5.11)]
- Otitis media and cardiovascular disorders in patients with Turner syndrome [see Warnings and Precautions (5.12)]
- Osteodystrophy in pediatric patients with chronic kidney disease [see Warnings and Precautions (5.13)]
- Lipoatrophy [see Warnings and Precautions (5.14)]
- Pancreatitis [see Warnings and Precautions (5.16)]

6.1 Clinical Trials Experience

Because clinical trials are conducted under varying conditions, adverse reaction rates observed during the clinical trials performed with one somatropin formulation cannot always be directly compared to the rates observed during the clinical trials performed with a second somatropin formulation, and may not reflect the adverse reaction rates observed in practice.

Pediatric Patients

Growth Hormone Deficiency (GHD)

Injection site discomfort has been reported. This is more commonly observed in children switched from another somatropin product to Nutropin AQ.

Turner Syndrome

In a randomized, controlled trial, there was a statistically significant increase, as compared to untreated controls, in otitis media (43% vs. 26%) and ear disorders (18% vs. 5%) in patients receiving somatropin.

Idiopathic Short Stature (ISS)

In a post-marketing surveillance study, the National Cooperative Growth Study (NCGS), the pattern of adverse events in over 8,000 patients with ISS was consistent with the known safety profile of growth hormone (GH), and no new safety signals attributable to GH were identified. The frequency of protocol-defined targeted adverse events is described in the table, below.

Table 1 Protocol-Defined Targeted Adverse Events in the ISS NCGS Cohort
Reported Events | NCGS (N = 8018)
Any Adverse Event
Overall | 103 (1.3%)
Targeted Adverse Event
Overall | 103 (1.3%)
Injection-site reaction | 28 (0.3%)
New onset or progression of scoliosis | 16 (0.2%)
Gynecomastia | 12 (0.1%)
Any new onset or recurring tumor (benign) | 12 (0.1%)
Arthralgia or arthritis | 10 (0.1%)
Diabetes mellitus | 5 (0.1%)
Edema | 5 (0.1%)
Cancer, neoplasm (new onset or recurrence) | 4 (0.0%)
Fracture | 4 (0.0%)
Intracranial hypertension | 4 (0.0%)
Abnormal bone or other growth | 3 (0.0%)
Central nervous system tumor | 2 (0.0%)
New or recurrent SCFE or AVN | 2 (0.0%)
Carpal tunnel syndrome | 1 (0.0%)
AVN = avascular necrosis; SCFE = slipped capital femoral epiphysis.
Data obtained with several rhGH products (Nutropin, Nutropin AQ, Nutropin Depot and Protropin).

In subjects treated in a long-term study of Nutropin for ISS, mean fasting and postprandial insulin levels increased, while mean fasting and postprandial glucose levels remained unchanged. Mean hemoglobin A1c (A1C) levels rose slightly from baseline as expected during adolescence; sporadic values outside normal limits occurred transiently.

Adult Patients

Growth Hormone Deficiency

In clinical studies with Nutropin AQ in GHD adults, edema or peripheral edema was reported in 41% of GH-treated patients and 25% of placebo-treated patients. In GHD adults, arthralgias and other joint disorders were reported in 27% of GH-treated patients and 15% of placebo-treated patients.

Nutropin therapy in adults with GHD of adult-onset was associated with an increase of median fasting insulin level in the Nutropin 0.0125 mg/kg/day group from 9.0 µU/mL at baseline to 13.0 µU/mL at Month 12 with a return to the baseline median level after a 3-week post-washout period of GH therapy. In the placebo group there was no change from 8.0 µU/mL at baseline to Month 12, and after the post-washout period, the median level was 9.0 µU/mL. The between-treatment group difference on the change from baseline to Month 12 in median fasting insulin level was significant, p < 0.0001. In childhood-onset subjects, there was an increase of median fasting insulin level in the Nutropin 0.025 mg/kg/day group from 11.0 µU/mL at baseline to 20.0 µU/mL at Month 12, in the Nutropin 0.0125 mg/kg/day group from 8.5 µU/mL to 11.0 µU/mL, and in the placebo group from 7.0 µU/mL to 8.0 µU/mL. The between-treatment group differences for these changes were significant, p = 0.0007.

In subjects with adult-onset GHD, there were no between-treatment group differences on change from baseline to Month 12 in mean A1C level, p = 0.08. In childhood-onset GHD, the mean A1C level increased in the Nutropin 0.025 mg/kg/day group from 5.2% at baseline to 5.5% at Month 12, and did not change in the Nutropin 0.0125 mg/kg/day group from 5.1% at baseline or in the placebo group from 5.3% at baseline. The between-treatment group differences were significant, p = 0.009.

6.2 Immunogenicity

As with all therapeutic proteins, there is potential for immunogenicity. The detection of antibody formation is highly dependent on the sensitivity and specificity of the assay. Additionally, the observed incidence of antibody (including neutralizing antibody) positivity in an assay may be influenced by several factors including assay methodology, sample handling, timing of sample collection, concomitant medications, and underlying disease. For these reasons, comparison of the incidence of antibodies to Nutropin with the incidence of antibodies to other products may be misleading. In the case of GH, antibodies with binding capacities lower than 2 mg/L have not been associated with growth attenuation. In a very small number of patients treated with somatropin, when binding capacity was greater than 2 mg/L, interference with the growth response was observed.

In clinical studies of pediatric patients that were treated with Nutropin for the first time, 0/107 GHD patients, 0/125 CKD patients, 0/112 TS, and 0/117 ISS patients screened for antibody production developed antibodies with binding capacities ≥ 2 mg/L at six months. In a clinical study of patients that were treated with Nutropin AQ for the first time, 0/38 GHD patients screened for antibody production for up to 15 months developed antibodies with binding capacities ≥ 2 mg/L.

Additional short-term immunologic and renal function studies were carried out in a group of pediatric patients with CKD after approximately one year of treatment to detect other potential adverse effects of antibodies to GH. Testing included measurements of C1q, C3, C4, rheumatoid factor, creatinine, creatinine clearance, and blood urea nitrogen (BUN). No adverse effects of GH antibodies were noted.

6.3 Post-Marketing Experience

The following adverse reactions have been identified during post approval use of somatropin or NUTROPIN AQ. Because these adverse events are reported voluntarily from a population of uncertain size, it is not always possible to reliably estimate their frequency or establish a causal relationship to drug exposure. The adverse events reported during post-marketing surveillance do not differ from those listed/discussed above in Sections 6.1 and 6.2 in children and adults.

Serious systemic hypersensitivity reactions including anaphylactic reactions and angioedema have been reported with postmarketing use of somatropin products [see Warnings and Precautions (5.6)].

Leukemia has been reported in a small number of GHD children treated with somatropin, somatrem (methionylated rhGH) and GH of pituitary origin. It is uncertain whether these cases of leukemia are related to GH therapy, the pathology of GHD itself, or other associated treatments such as radiation therapy. On the basis of current evidence, experts have not been able to conclude that GH therapy per se was responsible for these cases of leukemia. The risk for children with GHD, CKD, or TS, if any, remains to be established [see Contraindications (4) and Warnings and Precautions (5.3)].

The following additional adverse reactions have been reported in GH-treated patients: gynecomastia (children), and pancreatitis [Children and adults, see Warnings and Precautions (5.16)].

The following adverse reactions have been observed during the use of somatropin, including NUTROPIN AQ: Slipped capital femoral epiphysis [children, see Warnings and Precautions (5.10)] and osteonecrosis (children).

7 DRUG INTERACTIONS

7.1 11 β-Hydroxysteroid Dehydrogenase Type 1 (11βHSD-1)

The microsomal enzyme 11βHSD-1 is required for conversion of cortisone to its active metabolite, cortisol, in hepatic and adipose tissue. Growth hormone (GH) and somatropin inhibit 11βHSD-1. Consequently, individuals with untreated GH deficiency have relative increases in 11βHSD-1 and serum cortisol. Introduction of somatropin treatment may result in inhibition of 11βHSD-1 and reduced serum cortisol concentrations. As a consequence, previously undiagnosed central (secondary) hypoadrenalism may be unmasked and glucocorticoid replacement may be required in patients treated with somatropin. In addition, patients treated with glucocorticoid replacement for previously diagnosed hypoadrenalism may require an increase in their maintenance or stress doses following initiation of somatropin treatment; this may be especially true for patients treated with cortisone acetate and prednisone since conversion of these drugs to their biologically active metabolites is dependent on the activity of 11βHSD-1.

7.2 Pharmacologic Glucocorticoid Therapy and Supraphysiologic Glucocorticoid Treatment

Pharmacologic glucocorticoid therapy and supraphysiologic glucocorticoid treatment may attenuate the growth-promoting effects of somatropin in children. Therefore, glucocorticoid replacement therapy should be carefully adjusted in children with concomitant GH and glucocorticoid deficiency to avoid both hypoadrenalism and an inhibitory effect on growth.

The use of Nutropin AQ in patients with Chronic Kidney Disease (CKD) requiring glucocorticoid therapy has not been evaluated. Concomitant glucocorticoid therapy may inhibit the growth promoting effect of Nutropin AQ. Therefore, if glucocorticoid replacement is required for CKD, the glucocorticoid dose should be carefully adjusted to avoid an inhibitory effect on growth. In the clinical trials there was no evidence of drug interactions with Nutropin and commonly used drugs used in the management of CKD.

7.3 Cytochrome P450 (CYP450)-Metabolized Drugs

Limited published data indicate that somatropin treatment increases CYP450-mediated antipyrine clearance in man. These data suggest that somatropin administration may alter the clearance of compounds known to be metabolized by CYP450 liver enzymes (e.g., corticosteroids, sex steroids, anticonvulsants, cyclosporine). Careful monitoring is advisable when somatropin is administered in combination with other drugs known to be metabolized by CYP450 liver enzymes. However, formal drug interaction studies have not been conducted.

7.4 Oral Estrogen

Because oral estrogens may reduce insulin-like growth factor (IGF-1) response to somatropin treatment, girls and women receiving oral estrogen replacement may require greater somatropin dosages [see Dosage and Administration (2.2)].

7.5 Insulin and/or Oral/Injectable Hypoglycemic Agents

In patients with diabetes mellitus requiring drug therapy, the dose of insulin and/or oral/injectable hypoglycemic agents may require adjustment when somatropin therapy is initiated [see Warnings and Precautions (5.4)].

8 USE IN SPECIFIC POPULATIONS

8.1 Pregnancy

Pregnancy Category C. Animal reproduction studies have not been conducted with Nutropin AQ. It is also not known whether Nutropin AQ can cause fetal harm when administered to a pregnant woman or can affect reproduction capacity. Nutropin AQ should be given to a pregnant woman only if clearly needed.

8.3 Nursing Mothers

There have been no studies conducted with Nutropin AQ in nursing mothers. It is not known whether Nutropin AQ is excreted in human milk. Because many drugs are excreted in human milk, caution should be exercised when Nutropin AQ is administered to a nursing mother.

8.5 Geriatric Use

Clinical studies of Nutropin AQ did not include sufficient numbers of subjects aged 65 and over to determine whether they respond differently from younger subjects. Elderly patients may be more sensitive to the action of somatropin, and therefore may be more prone to develop adverse reactions. A lower starting dose and smaller dose increments should be considered for older patients [see Dosage and Administration (2.2)].

8.6 Hepatic Impairment

No studies have been conducted for Nutropin AQ in patients with hepatic impairment [see Clinical Pharmacology (12.3)].

8.7 Renal Impairment

Subjects with chronic renal failure tend to have decreased somatropin clearance compared to those with normal renal function [see Dosage and Administration (2.1) and Clinical Pharmacology (12.3)].

8.8 Gender Effect

No gender-specific pharmacokinetic studies have been done with Nutropin AQ. The available literature indicates that the pharmacokinetics of somatropin are similar in men and women.

10 OVERDOSAGE

Short Term

Short-term overdosage could lead initially to hypoglycemia and subsequently to hyperglycemia. Furthermore, overdose with somatropin is likely to cause fluid retention.

Long Term

Long-term overdosage could result in signs and symptoms of gigantism and/or acromegaly consistent with the known effects of excess growth hormone (GH) [see Dosage and Administration (2.2)].

11 DESCRIPTION

Nutropin AQ (somatropin) injection, for subcutaneous use is a human growth hormone (hGH) produced by recombinant DNA technology. Nutropin AQ has 191 amino acid residues and a molecular weight of 22,125 daltons. The amino acid sequence of the product is identical to that of pituitary-derived hGH. Nutropin AQ may contain not more than fifteen percent deamidated GH at expiration. The deamidated form of GH has been extensively characterized and has been shown to be safe and fully active.

Nutropin AQ is a sterile liquid intended for subcutaneous administration. The product is nearly isotonic at a concentration of 5 mg of GH per mL and has a pH of approximately 6.0.

Each pen cartridge or NuSpin contain either 5 mg, 10 mg or 20 mg of somatropin formulated in 17.4 mg sodium chloride, 5 mg phenol, 4 mg polysorbate 20, and 10 mM sodium citrate [see How Supplied/Storage and Handling (16)].

12 CLINICAL PHARMACOLOGY

12.1 Mechanism of Action

Somatropin (as well as endogenous growth hormone) binds to dimeric growth hormone receptors located within the cell membranes of target tissue cells resulting in intracellular signal transduction and a host of pharmacodynamic effects. Some of these pharmacodynamic effects are primarily mediated by insulin-like growth factor (IGF-1) produced in the liver and also locally (e.g., skeletal growth, protein synthesis), while others are primarily a consequence of the direct effects of somatropin (e.g., lipolysis) [see Clinical Pharmacology (12.2)].

12.2 Pharmacodynamics

In vitro and in vivo preclinical and clinical testing have demonstrated that Nutropin AQ is therapeutically equivalent to pituitary-derived hGH. Pediatric patients who lack adequate endogenous growth hormone (GH) secretion, patients with chronic kidney disease (CKD), and patients with Turner syndrome (TS) that were treated with Nutropin AQ or Nutropin resulted in an increase in growth rate and an increase in IGF-1 levels similar to that seen with pituitary-derived hGH.

Tissue Growth

A) Skeletal Growth: Nutropin AQ stimulates skeletal growth in pediatric patients with growth failure due to a lack of adequate secretion of endogenous GH or secondary to CKD and in patients with TS. Skeletal growth is accomplished at the epiphyseal plates at the ends of a growing bone. Growth and metabolism of epiphyseal plate cells are directly stimulated by GH and one of its mediators, IGF-I. Serum levels of IGF-I are low in children and adolescents who are GHD, but increase during treatment with somatropin. In pediatric patients, new bone is formed at the epiphyses in response to GH and IGF-I. This results in linear growth until these growth plates fuse at the end of puberty.
B) Cell Growth: Treatment with somatropin results in an increase in both the number and the size of skeletal muscle cells.
C) Organ Growth: GH influences the size of internal organs, including kidneys, and increases red cell mass. Treatment of hypophysectomized or genetic dwarf rats with somatropin results in organ growth that is proportional to the overall body growth. In normal rats subjected to nephrectomy-induced uremia, somatropin promoted skeletal and body growth.

Protein Metabolism

Linear growth is facilitated in part by GH-stimulated protein synthesis. This is reflected by nitrogen retention as demonstrated by a decline in urinary nitrogen excretion and blood urea nitrogen (BUN) during somatropin therapy.

Carbohydrate Metabolism

GH is a modulator of carbohydrate metabolism. For example, patients with inadequate secretion of GH sometimes experience fasting hypoglycemia that is improved by treatment with Nutropin AQ. Somatropin therapy may decrease insulin sensitivity. Untreated patients with CKD and TS have an increased incidence of glucose intolerance. Administration of somatropin to adults or children resulted in increases in serum fasting and postprandial insulin levels, more commonly in overweight or obese individuals. In addition, mean fasting and postprandial glucose and hemoglobin A1C levels remained in the normal range.

Lipid Metabolism

In GHD patients, administration of somatropin resulted in lipid mobilization, reduction in body fat stores, increased plasma fatty acids, and decreased plasma cholesterol levels.

Mineral Metabolism

The retention of total body potassium in response to somatropin administration apparently results from cellular growth. Serum levels of inorganic phosphorus may increase slightly in patients with inadequate secretion of endogenous GH, CKD, or TS during Nutropin AQ therapy due to metabolic activity associated with bone growth as well as increased tubular reabsorption of phosphate by the kidney. Serum calcium is not significantly altered in these patients. Sodium retention also occurs. Adults with childhood-onset GHD show low bone mineral density (BMD). Nutropin AQ therapy results in increases in serum alkaline phosphatase [see Warnings and Precautions (5.14)].

Connective Tissue Metabolism

GH stimulates the synthesis of chondroitin sulfate and collagen as well as the urinary excretion of hydroxyproline.

12.3 Pharmacokinetics

Absorption

The absolute bioavailability of somatropin after subcutaneous administration in healthy adult males has been determined to be 81 ± 20%. The mean terminal t1/2 after subcutaneous administration is significantly longer than that seen after intravenous administration (2.1 ± 0.43 hours vs. 19.5 ± 3.1 minutes) indicating that the subcutaneous absorption of the compound is slow and rate-limiting.

Distribution

Animal studies with somatropin showed that GH localizes to highly perfused organs, particularly the liver and kidney. The volume of distribution at steady state for somatropin in healthy adult males is about 50 mL/kg body weight, approximating the serum volume.

Metabolism

Both the liver and kidney have been shown to be important metabolizing organs for GH. Animal studies suggest that the kidney is the dominant organ of clearance. GH is filtered at the glomerulus and reabsorbed in the proximal tubules. It is then cleaved within renal cells into its constituent amino acids, which return to the systemic circulation.

Elimination

The mean terminal t1/2 after intravenous administration of somatropin in healthy adult males is estimated to be 19.5 ± 3.1 minutes. Clearance of rhGH after intravenous administration in healthy adults and children is reported to be in the range of 116–174 mL/hr/kg.

Bioequivalence of Formulations

Nutropin AQ has been determined to be bioequivalent to Nutropin based on the statistical evaluation of area under the curve (AUC) and maximum concentration (Cmax).

Special Populations

Pediatric: Available literature data suggests that somatropin clearances are similar in adults and children.

Geriatrics: Limited published data suggest that the plasma clearance and average steady-state plasma concentration of somatropin may not be different between young and elderly patients.

Race: Reported values for half-lives for endogenous GH in normal adult black males are not different from observed values for normal adult white males. No data for other races are available.

Growth Hormone Deficiency: Reported values for clearance of somatropin in adults and children with GHD range 138–245 mL/hr/kg and are similar to those observed in healthy adults and children. Mean terminal t1/2 values following intravenous and subcutaneous administration in adult and pediatric GHD patients are also similar to those observed in healthy adult males.

Chronic Kidney Disease: Children and adults with CKD and end-stage renal disease (ESRD) tend to have decreased clearance compared to normals. In a study with six pediatric patients 7 to 11 years of age, the clearance of Nutropin was reduced by 21.5% and 22.6% after the intravenous infusion and subcutaneous injection, respectively, of 0.05 mg/kg of Nutropin compared to normal healthy adults. Endogenous GH production may also increase in some individuals with ESRD. However, no somatropin accumulation has been reported in children with CKD or ESRD dosed with current regimens.

Turner Syndrome: No pharmacokinetic data are available for exogenously administered somatropin. However, reported half-lives, absorption, and elimination rates for endogenous GH in this population are similar to the ranges observed for normal subjects and GHD populations.

Hepatic Insufficiency: A reduction in somatropin clearance has been noted in patients with severe liver dysfunction. The clinical significance of this decrease is unknown.

Gender: No gender-specific pharmacokinetic studies have been done with Nutropin AQ. The available literature indicates that the pharmacokinetics of somatropin are similar in men and women.

Table 2 Summary of Nutropin AQ Pharmacokinetic Parameters in Healthy Adult Males 0.1 mg (approximately 0.3 IU [Based on current International Standard of 3 IU = 1 mg.])/kg SC
 | Cmax (µg/L) | Tmax (hr) | t1/2 (hr) | AUC0-∞ (μg ∙ hr/L) | CL/Fsc (mL/[hr ∙ kg])
MEAN [n = 36.] | 71.1 | 3.9 | 2.3 | 677 | 150
CV% | 17 | 56 | 18 | 13 | 13
Abbreviations: AUC0-∞ = area under the curve, Cmax = maximum concentration, CL/Fsc = systemic clearance, CV% = coefficient of variation in %; SC = subcutaneous, Fsc = subcutaneous bioavailability (not determined), t1/2 = half-life.

Figure 1
Single Dose Mean Growth Hormone Concentrations in Healthy Adult Males

13 NONCLINICAL TOXICOLOGY

13.1 Carcinogenesis, Mutagenesis, Impairment of Fertility

Carcinogenicity, mutagenicity, and reproduction studies have not been conducted with Nutropin AQ.

14 CLINICAL STUDIES

14.1 Pubertal Patients with Growth Hormone Deficiency (GHD)

One open label, multicenter, randomized clinical trial of two dosages of Nutropin was performed in pubertal patients with GHD. Ninety-seven patients (mean age 13.9 years, 83 male, 14 female) currently being treated with approximately 0.3 mg/kg/wk of GH were randomized to 0.3 mg/kg/wk or 0.7 mg/kg/wk Nutropin doses. All patients were already in puberty (Tanner stage ≥ 2) and had bone ages ≤ 14 years in males or ≤ 12 years in females. Mean baseline height standard deviation score (SDS) was –1.3.

The mean last measured height in all 97 patients after a mean duration of 2.7 ± 1.2 years, by analysis of covariance (ANCOVA) adjusting for baseline height, is shown below.

Table 3 Last Measured Height [Adjusted for baseline height] by Sex and Nutropin Dose for Pubertal Patients with GHD
 |  | Last Measured Height (cm) |  | Height Difference Between Groups (cm)
 | Age (yr) | 0.3 mg/kg/wk | 0.7 mg/kg/wk
 | Mean ± SD (range) | Mean ± SD | Mean ± SD | Mean ± SE
Male | 17.2 ± 1.3 (13.6 to 19.4) | 170.9 ± 7.9 (n = 42) | 174.5 ± 7.9 (n = 41) | 3.6 ± 1.7
Female | 15.8 ± 1.8 (11.9 to 19.3) | 154.7 ± 6.3 (n = 7) | 157.6 ± 6.3 (n = 7) | 2.9 ± 3.4

The mean height SDS at last measured height (n = 97) was –0.7 ± 1.0 in the 0.3 mg/kg/wk group and – 0.1 ± 1.2 in the 0.7 mg/kg/wk group. For patients completing 3.5 or more years (mean 4.1 years) of Nutropin treatment (15/49 patients in the 0.3 mg/kg/wk group and 16/48 patients in the 0.7 mg/kg/wk group), the mean last measured height was 166.1 ± 8.0 cm in the 0.3 mg/kg/wk group and 171.8 ± 7.1 cm in the 0.7 mg/kg/wk group, adjusting for baseline height and sex.

The mean change in bone age was approximately one year for each year in the study in both dose groups. Patients with baseline height SDS above –1.0 were able to attain normal adult heights with the 0.3 mg/kg/wk dose of Nutropin (mean height SDS at near-adult height = –0.1, n = 15).

Thirty-one patients had bone mineral density (BMD) determined by dual energy x-ray absorptiometry (DEXA) scans at study conclusion. The two dose groups did not differ significantly in mean SDS for total body BMD (–0.9 ± 1.9 in the 0.3 mg/kg/wk group vs. –0.8 ± 1.2 in the 0.7 mg/kg/wk group, n = 20) or lumbar spine BMD (–1.0 ± 1.0 in the 0.3 mg/kg/wk group vs. –0.2 ± 1.7 in the 0.7 mg/kg/wk group, n = 21).

Over a mean duration of 2.7 years, patients in the 0.7 mg/kg/wk group were more likely to have IGF-I values above the normal range than patients in the 0.3 mg/kg/wk group (27.7% vs. 9.0% of IGF-I measurements for individual patients). The clinical significance of elevated IGF-I values is unknown.

14.2 Pediatric Patients with Growth Failure Secondary to Chronic Kidney Disease (CKD)

Two multicenter, randomized, controlled clinical trials were conducted to determine whether treatment with Nutropin prior to renal transplantation in patients with CKD could improve their growth rates and height deficits. One study was a double-blind, placebo-controlled trial and the other was an open-label, randomized trial. The dose of Nutropin in both controlled studies was 0.05 mg/kg/day (0.35 mg/kg/week) administered daily by subcutaneous injection. Combining the data from those patients completing two years in the two controlled studies results in 62 patients treated with Nutropin and 28 patients in the control groups (either placebo-treated or untreated). The mean first year growth rate was 10.8 cm/yr for Nutropin-treated patients, compared with a mean growth rate of 6.5 cm/yr for placebo/untreated controls (p < 0.00005). The mean second year growth rate was 7.8 cm/yr for the Nutropin-treated group, compared with 5.5 cm/yr for controls (p < 0.00005). There was a significant increase in mean height SDS in the Nutropin group (–2.9 at baseline to –1.5 at Month 24, n = 62) but no significant change in the controls (-2.8 at baseline to –2.9 at Month 24, n = 28). The mean third year growth rate of 7.6 cm/yr in the Nutropin-treated patients (n = 27) suggests that Nutropin stimulates growth beyond two years. However, there are no control data for the third year because control patients crossed over to Nutropin treatment after two years of participation. The gains in height were accompanied by appropriate advancement of skeletal age. These data demonstrate that Nutropin therapy improves growth rate and corrects the acquired height deficit associated with CKD.

The North American Pediatric Renal Transplant Cooperative Study (NAPRTCS) has reported data for growth post-transplant in children who did not receive GH prior to transplantation as well as children who did receive Nutropin during the clinical trials prior to transplantation. The average change in height SDS during the initial two years post-transplant was 0.15 for the 2,391 patients who did not receive GH pre-transplant and 0.28 for the 57 patients who did^1. For patients who were followed for 5 years post-transplant, the corresponding changes in height SDS were also similar between groups.

14.3 Pediatric Patients with Turner Syndrome (TS)

Three US studies, two long-term, open-label, multicenter, historically controlled studies (Studies 1 and 2), and one long-term, randomized, dose-response study (Study 3) and one Canadian, long-term, randomized, open-label, multicenter, concurrently controlled study, were conducted to evaluate the efficacy of somatropin treatment of short stature due to TS.

In the US Studies 1 and 2, the effect of long-term GH treatment (0.375 mg/kg/week given either 3 times per week or daily) on adult height was determined by comparing adult heights in the treated patients with those of age-matched historical controls with TS who received no growth-promoting therapy. In Study 1, estrogen treatment was delayed until patients were at least age 14. GH therapy resulted in a mean adult height gain of 7.4 cm (mean duration of GH therapy of 7.6 years) vs. matched historical controls by ANCOVA.

In Study 2, patients treated with early Nutropin therapy (before 11 years of age) were randomized to receive estrogen-replacement therapy (conjugated estrogens, 0.3 mg escalating to 0.625 mg daily) at either age 12 or 15 years. Compared with matched historical controls, early Nutropin therapy (mean duration of 5.6 years) combined with estrogen replacement at age 12 years resulted in an adult height gain of 5.9 cm (n = 26), whereas girls who initiated estrogen at age 15 years (mean duration of Nutropin therapy 6.1 years) had a mean adult height gain of 8.3 cm (n = 29). Patients who initiated Nutropin after age 11 (mean age 12.7 years; mean duration of Nutropin therapy 3.8 years) had a mean adult height gain of 5.0 cm (n = 51).

Thus, in Studies 1 and 2, the greatest improvement in adult height was observed in patients who received early GH treatment and estrogen after age 14 years.

In Study 3, a randomized, blinded dose-response study, patients were treated from a mean age of 11.1 years for a mean duration of 5.3 years with a weekly GH dose of either 0.27 mg/kg or 0.36 mg/kg administered in divided doses 3 or 6 times weekly. The mean near-final height of GH-treated patients was 148.7 ± 6.5 cm (n = 31). When compared to historical control data, the mean gain in adult height was approximately 5 cm.

The Canadian randomized study compared near-adult height outcomes for GH-treated patients to those of a concurrent control group who received no injections. The somatropin-treated patients received a dosage of 0.3 mg/kg/week given in divided doses 6 times per week from a mean age of 11.7 years for a mean duration of 4.7 years. Puberty was induced with a standardized estrogen regimen initiated at 13 years of age for both treatment groups. The somatropin-treated group (n = 27) attained a mean (± SD) near final height of 146.0 ± 6.2 cm; the untreated control group (n = 19) attained a near final height of 142.1 ± 4.8 cm. By ANCOVA (with adjustments for baseline height and mid-parental height), the effect of GH-treatment was a mean height increase of 5.4 cm (p = 0.001).

In summary, patients with TS (total n = 181 from the 4 studies above) treated to adult height achieved statistically significant average height gains ranging from 5.0–8.3 cm.

Table 4 Summary of Efficacy Results in Turner Syndrome [Data shown are mean values.]
Study | Group | Study Design [RCT: randomized controlled trial; MHT: matched historical controlled trial; RDT: randomized dose-response trial.] | N at Adult Height | GH Age (yr) | Estrogen Age (yr) | GH Duration (yr) | Adult Height Gain (cm) [Analysis of covariance vs. controls.]
US 1 |  | MHT | 17 | 9.1 | 15.2 | 7.6 | 7.4
US 2 | A [A = GH age < 11 yr, estrogen age 15 yr. B = GH age < 11 yr, estrogen age 12 yr. C = GH age > 11 yr, estrogen at Month 12.] | MHT | 29 | 9.4 | 15.0 | 6.1 | 8.3
 | B |  | 26 | 9.6 | 12.3 | 5.6 | 5.9
 | C |  | 51 | 12.7 | 13.7 | 3.8 | 5.0
US 3 |  | RDT | 31 | 11.1 | 8–13.5 | 5.3 | ~5 [Compared with historical data.]
Canadian |  | RCT | 27 | 11.7 | 13 | 4.7 | 5.4

14.4 Pediatric Patient with Idiopathic Short Stature (ISS)

A long-term, open-label, multicenter study was conducted to examine the safety and efficacy of Nutropin in pediatric patients with ISS, also called non-growth hormone deficient short stature. For the first year, 122 pre-pubertal subjects over the age of 5 years with stimulated serum GH ≥ 10 ng/mL were randomized into two treatment groups of approximately equal size; one group was treated with Nutropin 0.3 mg/kg weekly divided into three doses per week and the other group served as untreated controls. For the second and subsequent years of the study, all subjects were re-randomized to receive the same total weekly dose of Nutropin (0.3 mg/kg weekly) administered either daily or three times weekly. Treatment with Nutropin was continued until a subject's bone age was > 15.0 years (boys) or > 14.0 years (girls) and the growth rate was < 2 cm/yr, after which subjects were followed until adult height was achieved. The mean baseline values were: height SDS–2.8, IGF-I SDS -0.9, age 9.4 years, bone age 7.8 years, growth rate 4.4 cm/yr, mid-parental target height SDS –0.7, and Bayley-Pinneau predicted adult height SDS –2.3. Nearly all subjects had predicted adult height that was less than mid-parental target height.

During the one-year controlled phase of the study, the mean height velocity increased by 0.5 ± 1.8 cm (mean ± SD) in the no-treatment control group and by 3.1 ± 1.7 cm in the Nutropin group (p < 0.0001). For the same period of treatment the mean height SDS increased by 0.4 ± 0.2 and remained unchanged (0.0 ± 0.2) in the control group (p < 0.001).

Of the 118 subjects who were treated with Nutropin (70%) reached near-adult height (hereafter called adult height) after 2–10 years of Nutropin therapy. Their last measured height, including post-treatment follow-up, was obtained at a mean age of 18.3 years in males and 17.3 years in females. The mean duration of therapy was 6.2 and 5.5 years, respectively. Adult height was greater than pretreatment predicted adult height in 49 of 60 males (82%) and 19 of 23 females (83%). The mean difference between adult height and pretreatment predicted adult height was 5.2 cm (2.0 inches) in males and 6.0 cm (2.4 inches) in females (p < 0.0001 for both). The table (below) summarizes the efficacy data.

Table 5 Long-Term Efficacy in ISS (Mean ± SD)
Characteristic | Males (n = 60) | Females (n = 23)
Adult height (cm) | 166.3 ± 5.8 | 153.1 ± 4.8
Pretreatment predicted adult height (cm) | 161.1 ± 5.5 | 147.1 ± 5.1
Adult height minus pretreatment predicted adult height (cm) | + 5.2 ± 5.0 [p < 0.0001 versus zero.] | + 6.0 ± 5.0
Adult height SDS | –1.5 ± 0.8 | –1.6 ± 0.7
Pretreatment predicted adult height SDS | –2.2 ± 0.8 | –2.5 ± 0.8
Adult height minus pretreatment predicted adult height SDS | + 0.7 ± 0.7 | + 0.9 ± 0.8

Nutropin therapy resulted in an increase in mean IGF-I SDS from –0.9 ± 1.0 to –0.2 ± 0.9 in Treatment Year 1. During continued treatment, mean IGF-I levels remained close to the normal mean. IGF-I SDS above + 2 occurred sporadically in 14 subjects.

14.5 Adult Growth Hormone Deficiency

Two multicenter, double-blind, placebo-controlled clinical trials were conducted in growth hormone-deficient adults. Study 1 was conducted in subjects with adult-onset GHD (n = 166), mean age 48.3 years, at doses of 0.0125 or 0.00625 mg/kg/day; doses of 0.025 mg/kg/day were not tolerated in these subjects. Study 2 was conducted in previously treated subjects with childhood-onset GHD (n = 64), mean age 23.8 years, at randomly assigned doses of 0.025 or 0.0125 mg/kg/day. The studies were designed to assess the effects of replacement therapy with Nutropin on body composition.

Significant changes from baseline to Month 12 of treatment in body composition (i.e., total body % fat mass, trunk % fat mass, and total body % lean mass by DEXA scan) were seen in all Nutropin groups in both studies (p < 0.0001 for change from baseline and vs. placebo), whereas no statistically significant changes were seen in either of the placebo groups. In the adult-onset study, the Nutropin group improved mean total body fat from 35.0% to 31.5%, mean trunk fat from 33.9% to 29.5%, and mean lean body mass from 62.2% to 65.7%, whereas the placebo group had mean changes of 0.2% or less (p = not significant). Due to the possible effect of GH-induced fluid retention on DEXA measurements of lean body mass, DEXA scans were repeated approximately 3 weeks after completion of therapy; mean % lean body mass in the Nutropin group was 65.0%, a change of 2.8% from baseline, compared with a change of 0.4% in the placebo group (p < 0.0001 between groups).

In the childhood-onset study, the high-dose Nutropin group improved mean total body fat from 38.4% to 32.1%, mean trunk fat from 36.7% to 29.0%, and mean lean body mass from 59.1% to 65.5%; the low-dose Nutropin group improved mean total body fat from 37.1% to 31.3%, mean trunk fat from 37.9% to 30.6%, and mean lean body mass from 60.0% to 66.0%; the placebo group had mean changes of 0.6% or less (p = not significant).

Table 6 Mean Changes from Baseline to Month 12 in Proportion of Fat and Lean by DEXA for Adult- and Childhood- Onset GHD Studies
 | Adult Onset (Study 1) |  |  | Childhood Onset (Study 2)
Proportion | Placebo (n = 62) | Nutropin (n = 63) | Between-Groups t-test p-value | Placebo (n = 13) | Nutropin 0.0125 mg/kg/day (n = 15) | Nutropin 0.025 mg/kg/day (n = 15) | Placebo vs. Pooled Nutropin t-test p-value
Total body percent fat
Baseline | 36.8 | 35.0 | 0.38 | 35.0 | 37.1 | 38.4 | 0.45
Month 12 | 36.8 | 31.5 | — | 35.2 | 31.3 | 32.1 | —
Baseline to Month 12 change | -0.1 | -3.6 | < 0.0001 | + 0.2 | -5.8 | -6.3 | < 0.0001
Post-washout | 36.4 | 32.2 | — | NA | NA | NA | —
Baseline to post-washout change | -0.4 | -2.8 | < 0.0001 | NA | NA | NA | —
Trunk percent fat
Baseline | 35.3 | 33.9 | 0.50 | 32.5 | 37.9 | 36.7 | 0.23
Month 12 | 35.4 | 29.5 | — | 33.1 | 30.6 | 29.0 | —
Baseline to Month 12 change | 0.0 | -4.3 | < 0.0001 | + 0.6 | -7.3 | -7.6 | < 0.0001
Post-washout | 34.9 | 30.5 | — | NA | NA | NA | —
Baseline to post-washout change | -0.3 | -3.4 | — | NA | NA | NA | —
Total body percent lean
Baseline | 60.4 | 62.2 | 0.37 | 62.0 | 60.0 | 59.1 | 0.48
Month 12 | 60.5 | 65.7 | — | 61.8 | 66.0 | 65.5 | —
Baseline to Month 12 change | + 0.2 | + 3.6 | < 0.0001 | -0.2 | + 6.0 | + 6.4 | < 0.0001
Post-washout | 60.9 | 65.0 | — | NA | NA | NA | —
Baseline to post-washout change | + 0.4 | + 2.8 | < 0.0001 | NA | NA | NA | —
NA = not available

In the adult-onset study, significant decreases from baseline to Month 12 in low-density lipoprotein (LDL) cholesterol and LDL:high-density lipoprotein (HDL) ratio were seen in the Nutropin group compared to the placebo group, p < 0.02; there were no statistically significant between-group differences in change from baseline to Month 12 in total cholesterol, HDL cholesterol, or triglycerides. In the childhood-onset study significant decreases from baseline to Month 12 in total cholesterol, LDL cholesterol, and LDL:HDL ratio were seen in the high-dose Nutropin group only, compared to the placebo group, p < 0.05. There were no statistically significant between-group differences in HDL cholesterol or triglycerides from baseline to Month 12.

In the childhood-onset study, 55% of the patients had decreased spine BMD (z-score < –1) at baseline. The administration of Nutropin (n = 16) (0.025 mg/kg/day) for two years resulted in increased spine BMD from baseline when compared to placebo (n = 13) (4.6% vs. 1.0%, respectively, p < 0.03); a transient decrease in spine BMD was seen at six months in the Nutropin-treated patients. Thirty-five percent of subjects treated with this dose had supraphysiological levels of IGF-I at some point during the study, which may carry unknown risks. No significant improvement in total body BMD was found when compared to placebo. A lower GH dose (0.0125 mg/kg/day) did not show significant increments in either of these bone parameters when compared to placebo. No statistically significant effects on BMD were seen in the adult-onset study where patients received GH (0.0125 mg/kg/day) for one year.

Muscle strength, physical endurance, and quality of life measurements were not markedly abnormal at baseline, and no statistically significant effects of Nutropin therapy were observed in the two studies.

A subsequent 32-week, multicenter, open-label, controlled clinical trial was conducted using Nutropin AQ, Nutropin Depot, or no treatment in adults with both adult-onset and childhood-onset GHD. Subjects were randomized into the three groups to evaluate effects on body composition, including change in visceral adipose tissue (VAT) as determined by computed tomography (CT) scan.

For subjects evaluable for change in VAT in the Nutropin AQ (n = 44) and untreated (n = 19) groups, the mean age was 46.2 years and 78% had adult-onset GHD. Subjects in the Nutropin AQ group were treated at doses up to 0.012 mg/kg per day in women (all of whom received estrogen replacement therapy) and men under age 35 years, and up to 0.006 mg/kg per day in men over age 35 years.

The mean absolute change in VAT from baseline to Week 32 was –10.7 cm^2 in the Nutropin AQ group and + 8.4 cm^2 in the untreated group (p = 0.013 between groups). There was a 6.7% VAT loss in the Nutropin AQ group (mean percent change from baseline to Week 32) compared with a 7.5% increase in the untreated group (p = 0.012 between groups). The effect of reducing VAT in adult GHD patients with Nutropin AQ on long-term cardiovascular morbidity and mortality has not been determined.

Table 7 Visceral Adipose Tissue by Computed Tomography Scan: Percent Change and Absolute Change from Baseline to Week 32 in Study 3
 | Nutropin AQ (n = 44) | Untreated (n = 19) | Treatment Difference (adjusted mean) | p-value
Baseline VAT (cm^2) (mean) | 126.2 | 123.3
Change in VAT (cm^2) (adjusted mean) | – 10.7 | + 8.4 | – 19.1 | 0.013 [ANCOVA using baseline VAT as a covariate]
Percent change in VAT (adjusted mean) | – 6.7 | + 7.5 | – 14.2 | 0.012
VAT = visceral adipose tissue.

16 HOW SUPPLIED/STORAGE AND HANDLING

Pen Cartridge (2 mL): | 10 mg 20 mg | NDC 50242-043-14 NDC 50242-073-01
Nutropin AQ NuSpin (2 mL): | 5 mg 10 mg 20 mg | NDC 50242-075-01 NDC 50242-074-01 NDC 50242-076-01

Storage and Handling

Nutropin AQ cartridge and NuSpin injection device contents are stable for 28 days after initial use when stored at 2–8°C/36–46°F (under refrigeration). Avoid freezing Nutropin AQ in the cartridge or NuSpin injection device. Nutropin AQ is light sensitive and the cartridges and Nutropin AQ NuSpin should be protected from light. Store the cartridge and Nutropin AQ NuSpin injection device refrigerated in a dark place when they are not in use.

17 PATIENT COUNSELING INFORMATION

Patients being treated with Nutropin AQ (and/or their parents) should be informed about the potential benefits and risks associated with Nutropin AQ treatment, including a review of the contents of the INSTRUCTIONS FOR USE. This information is intended to better educate patients (and caregivers); it is not a disclosure of all possible adverse or intended effects.

Patients and caregivers who will administer Nutropin AQ should receive appropriate training and instruction on the proper use of Nutropin AQ from the physician or other suitably qualified health care professional. A puncture-resistant container for the disposal of used syringes and needles should be strongly recommended. Patients and/or parents should be thoroughly instructed in the importance of proper disposal, and cautioned against any reuse of needles and syringes. This information is intended to aid in the safe and effective administration of the medication.

Please see the accompanying directions for use of the delivery device.

Nutropin AQ®
(somatropin) injection, for subcutaneous use
Manufactured by:
Genentech, Inc.
A Member of the Roche Group
1 DNA Way
South San Francisco, CA 94080–4990

Nutropin AQ® is a registered trademark of
Genentech, Inc.
©2025 Genentech, Inc.

Representative sample of labeling (see the HOW SUPPLIED section for complete listing):

INSTRUCTIONS FOR USE

Nutropin AQ® NuSpin® 5
(somatropin) injection, for subcutaneous use

Genentech
Rx only

INSTRUCTIONS FOR USE

Description: The Nutropin AQ NuSpin 5 is a multi-dose, dial-a-dose injection device prefilled with Nutropin AQ (somatropin) injection, for subcutaneous use. It features automatic injection of the drug and is disposable. The Nutropin AQ NuSpin 5 (Clear Color, 5 mg/2 mL) delivers doses from 0.05 to 1.75 mg in increments of 0.05 mg.

Intended Use: The Nutropin AQ NuSpin 5 is intended to be used by a healthcare professional or patient to deliver Nutropin AQ (somatropin) injection, for subcutaneous use, from an injection device. The device can be used in any setting, including the home, and is disposable.

IMPORTANT NOTES

- Always follow the directions of your healthcare professional and the instructions provided on the back. Contact your healthcare professional if you have any questions.
- Check the label on the NuSpin 5 to make sure the medicine matches your prescription and it has not expired.
- Inspect the cartridge before use to ensure that the medicine in it is clear. If it is cloudy or hazy, do not inject. Return the NuSpin 5 to your healthcare professional.
- Store your NuSpin 5 inside the refrigerator at 2–8°C (36–46°F). Protect from light.

- The product can be used for 28 days after it has been primed and kept under proper storage conditions.
- For the first use of each NuSpin 5, always follow the New NuSpin 5 Set Up Instructions to ensure that air is expelled from the cartridge.
- Do not store with the needle attached. The needle should be removed and safely disposed of immediately after use.
- Keep NuSpin and all medicines out of the reach of young children.

FREQUENTLY ASKED QUESTIONS

1. What type of needles should be used?
  Your Healthcare Professional will recommend a needle that is appropriate for you. The following needles will fit and work on the Nutropin AQ NuSpin:
  - BD Ultra-Fine™ 29 g × 1/2 inch (12.7 mm)
  - BD Ultra-Fine™ Ill short pen needle 31 g × 5/16 inch (8 mm)
  - NovoFine® Autocover® 30 g (8 mm)
  Pen needles from other countries may not fit on your NuSpin device. If you travel outside the United States, make sure you take enough needles for the duration of your stay.
2. Do I need to change the needle every time I use my Nutropin AQ NuSpin?
  Yes. A new needle must be used for every injection. The needle is sterile only for one single injection.
3. Do I need to prime the Nutropin AQ NuSpin each time?
  No. The NuSpin 5 only needs to be primed once, at first use. After the first use of each NuSpin 5, follow the instructions and skip Step 2.
4. When and how do I dispose of my Nutropin AQ NuSpin?
  Your NuSpin 5 is prefilled and the cartridge cannot be replaced. When your NuSpin 5 is empty, dispose of the entire NuSpin 5 as instructed by your healthcare professional. If the empty NuSpin 5 is disposed of with the needle attached, discard the entire device using the same procedure as for needle disposal.

5. Where should I store my Nutropin AQ NuSpin?
  When not in use, your NuSpin 5 should be stored inside a refrigerator at 2–8°C (36–46°F) to maintain the potency of Nutropin AQ (somatropin) injection, for subcutaneous use. During use, we recommend that you have your NuSpin 5 outside of the refrigerator for no longer than one hour per day. When traveling, place your NuSpin 5 in a water-resistant container before placing in a cooler.
  DO NOT FREEZE. KEEP DRY.
6. What should I do if my Nutropin AQ NuSpin is dropped or damaged?
  If you drop the NuSpin 5, check to see if it is damaged. You should also check to see that the black dose knob and the Activator are moving properly. If you notice the NuSpin 5 is damaged, contact your healthcare professional or call 1-866-NUTROPIN for advice.
7. What should I do if my Nutropin AQ NuSpin needs cleaning?
  Use a damp cloth to wipe away dirt. Do not place underwater. Do not use alcohol.

Genentech, Inc., A Member of the Roche Group
1 DNA Way, South San Francisco, CA 94080-4990
Initial US Approval January 2008
NuSpin® is a registered trademark of Genentech, Inc.
Copyright © 2016 Genentech, Inc.

INSTRUCTIONS FOR USE
NEW NuSpin 5 SET UP: STEP-BY-STEP INSTRUCTIONS FOR THE FIRST USE OF EACH NEW NUTROPIN AQ NuSpin 5
STEP 1: Attach the needle |  | STEP 2: Prime the Nutropin AQ NuSpin
Before you begin, wash your hands. Twist gently and pull to remove the NuSpin 5 cap. Inspect the cartridge before use to ensure that the medicine in it is clear. If it is cloudy or hazy, do not inject. Open a new needle by peeling off the paper tab from the needle package. | Attach the needle by carefully screwing the needle onto the needle holder. Do not overtighten. Remove both protective covers from the needle and save the outer cover. | Turn the dose knob to the ℗ position in the dose window. It may take multiple clicks to get to ℗. Hold the NuSpin 5 with the needle pointing upwards. Gently tap the cartridge holder to move any air bubbles to the NuSpin 5 tip. | Slide the Activator toward the needle. If you do not see fluid at the needle tip, redial to and slide the Activator forward again. Repeat until you see fluid.

ROUTINE USE: DOSING AND ADMINISTRATION
STEP 3: Set the dose |  | STEP 4: Give the injection |  | Check dose given
Make sure the dose window reads . Turn the dose knob until the dose prescribed by your healthcare professional appears in the dose window. | If your dose is "between" two numbers in the dose window, the between those two numbers indicates your dose. Turn the dose knob to . The ℗ position indicates a 0.35 mg dose on your NuSpin 5. If you turn the dose knob too far, simply turn it back to the correct dose. (Example above shows a dose of 0.05 mg, represented by). | Select and prepare your injection site as instructed by your healthcare professional. Position your hand so you can easily slide the Activator. Push the needle into the skin. | Slide the Activator toward the needle. Hold the Activator down until the dose knob returns to and continue to hold in place for 5 seconds. Withdraw the Nutropin AQ NuSpin 5 until the needle is removed from the skin. If the dose knob returns to , you have received your full dose. | If the dose knob stops before it returns to , your Nutropin AQ NuSpin 5 is empty and you have not received your full dose. The number shown in the dose window is the amount needed to obtain a full dose. Your healthcare professional will advise you on the procedure for using the last dose in the NuSpin 5.
REMOVAL AND DISPOSAL OF THE NEEDLE
Carefully place the outer cover of the needle package over the needle, unscrew, and dispose of it as instructed by your healthcare professional.
STORAGE AND NEXT USE
Replace the cap and store your NuSpin 5 inside the refrigerator at 2–8°C (36–46°F). Protect from light. For the next use, it is already primed. Follow the instructions and skip Step 2.
Genentech

INSTRUCTIONS FOR USE

Nutropin AQ® NuSpin® 10
(somatropin) injection, for subcutaneous use

Genentech
Rx only

INSTRUCTIONS FOR USE

Description: The Nutropin AQ NuSpin 10 is a multi-dose, dial-a-dose injection device prefilled with Nutropin AQ (somatropin) injection, for subcutaneous use. It features automatic injection of the drug and is disposable. The Nutropin AQ NuSpin 10 (Teal Color, 10 mg/2 mL) delivers doses from 0.1 to 3.5 mg in increments of 0.1 mg.

Intended Use: The Nutropin AQ NuSpin 10 is intended to be used by a healthcare professional or patient to deliver Nutropin AQ (somatropin) injection, for subcutaneous use, from an injection device. The device can be used in any setting, including the home, and is disposable.

IMPORTANT NOTES

- Always follow the directions of your healthcare professional and the instructions provided on the back. Contact your healthcare professional if you have any questions.
- Check the label on the NuSpin 10 to make sure the medicine matches your prescription and it has not expired.
- Inspect the cartridge before use to ensure that the medicine in it is clear. If it is cloudy or hazy, do not inject. Return the NuSpin 10 to your healthcare professional.
- Store your NuSpin 10 inside the refrigerator at 2–8°C (36–46°F). Protect from light.

- The product can be used for 28 days after it has been primed and kept under proper storage conditions.
- For the first use of each NuSpin 10, always follow the New NuSpin 10 Set Up Instructions to ensure that air is expelled from the cartridge.
- Do not store with the needle attached. The needle should be removed and safely disposed of immediately after use.
- Keep NuSpin and all medicines out of the reach of young children.

FREQUENTLY ASKED QUESTIONS

1. What type of needles should be used?
  Your Healthcare Professional will recommend a needle that is appropriate for you. The following needles will fit and work on the Nutropin AQ NuSpin:
  - BD Ultra-Fine™ 29 g × 1/2 inch (12.7 mm)
  - BD Ultra-Fine™ Ill short pen needle 31 g × 5/16 inch (8 mm)
  - NovoFine® Autocover® 30 g (8 mm)
  Pen needles from other countries may not fit on your NuSpin device. If you travel outside the United States, make sure you take enough needles for the duration of your stay.
2. Do I need to change the needle every time I use my Nutropin AQ NuSpin?
  Yes. A new needle must be used for every injection. The needle is sterile only for one single injection.
3. Do I need to prime the Nutropin AQ NuSpin each time?
  No. The NuSpin 10 only needs to be primed once, at first use. After the first use of each NuSpin 10, follow the instructions and skip Step 2.
4. When and how do I dispose of my Nutropin AQ NuSpin?
  Your NuSpin 10 is prefilled and the cartridge cannot be replaced. When your NuSpin 10 is empty, dispose of the entire NuSpin 10 as instructed by your healthcare professional. If the empty NuSpin 10 is disposed of with the needle attached, discard the entire device using the same procedure as for needle disposal.

5. Where should I store my Nutropin AQ NuSpin?
  When not in use, your NuSpin 10 should be stored inside a refrigerator at 2–8°C (36–46°F) to maintain the potency of Nutropin AQ (somatropin) injection, for subcutaneous use. During use, we recommend that you have your NuSpin 10 outside of the refrigerator for no longer than one hour per day. When traveling, place your NuSpin 10 in a water-resistant container before placing in a cooler.
  DO NOT FREEZE. KEEP DRY.
6. What should I do if my Nutropin AQ NuSpin is dropped or damaged?
  If you drop the NuSpin 10, check to see if it is damaged. You should also check to see that the black dose knob and the Activator are moving properly. If you notice the NuSpin 10 is damaged, contact your healthcare professional or call 1-866-NUTROPIN for advice.
7. What should I do if my Nutropin AQ NuSpin needs cleaning?
  Use a damp cloth to wipe away dirt. Do not place underwater. Do not use alcohol.

Genentech, Inc., A Member of the Roche Group
1 DNA Way, South San Francisco, CA 94080-4990
Initial US Approval January 2008
NuSpin® is a registered trademark of Genentech, Inc.
Copyright © 2016 Genentech, Inc.

INSTRUCTIONS FOR USE
NEW NuSpin 10 SET UP: STEP-BY-STEP INSTRUCTIONS FOR THE FIRST USE OF EACH NEW NUTROPIN AQ NuSpin 10
STEP 1: Attach the needle |  | STEP 2: Prime the Nutropin AQ NuSpin
Before you begin, wash your hands. Twist gently and pull to remove the NuSpin 10 cap. Inspect the cartridge before use to ensure that the medicine in it is clear. If it is cloudy or hazy, do not inject. Open a new needle by peeling off the paper tab from the needle package. | Attach the needle by carefully screwing the needle onto the needle holder. Do not overtighten. Remove both protective covers from the needle and save the outer cover. | Turn the dose knob to the ℗ position in the dose window. It may take multiple clicks to get to ℗. Hold the NuSpin 10 with the needle pointing upwards. Gently tap the cartridge holder to move any air bubbles to the NuSpin 10 tip. | Slide the Activator toward the needle. If you do not see fluid at the needle tip, redial to and slide the Activator forward again. Repeat until you see fluid.

ROUTINE USE: DOSING AND ADMINISTRATION
STEP 3: Set the dose |  | STEP 4: Give the injection |  | Check dose given
Make sure the dose window reads . Turn the dose knob until the dose prescribed by your healthcare professional appears in the dose window. | If your dose is "between" two numbers in the dose window, the between those two numbers indicates your dose. Turn the dose knob to . The ℗ position indicates a 0.7 mg dose on your NuSpin 10. If you turn the dose knob too far, simply turn it back to the correct dose. (Example above shows a dose of 0.1 mg, represented by). | Select and prepare your injection site as instructed by your healthcare professional. Position your hand so you can easily slide the Activator. Push the needle into the skin. | Slide the Activator toward the needle. Hold the Activator down until the dose knob returns to and continue to hold in place for 5 seconds. Withdraw the Nutropin AQ NuSpin 10 until the needle is removed from the skin. If the dose knob returns to , you have received your full dose. | If the dose knob stops before it returns to , your Nutropin AQ NuSpin 10 is empty and you have not received your full dose. The number shown in the dose window is the amount needed to obtain a full dose. Your healthcare professional will advise you on the procedure for using the last dose in the NuSpin 10.
REMOVAL AND DISPOSAL OF THE NEEDLE
Carefully place the outer cover of the needle package over the needle, unscrew, and dispose of it as instructed by your healthcare professional.
STORAGE AND NEXT USE
Replace the cap and store your NuSpin 10 inside the refrigerator at 2–8°C (36–46°F). Protect from light. For the next use, it is already primed. Follow the instructions and skip Step 2.
Genentech

INSTRUCTIONS FOR USE

Nutropin AQ® NuSpin® 20
(somatropin) injection, for subcutaneous use

Genentech
Rx only

INSTRUCTIONS FOR USE

Description: The Nutropin AQ NuSpin 20 is a multi-dose, dial-a-dose injection device prefilled with Nutropin AQ (somatropin) injection, for subcutaneous use. It features automatic injection of the drug and is disposable. The Nutropin AQ NuSpin 20 (Blue Color, 20 mg/2 mL) delivers doses from 0.2 to 7.0 mg in increments of 0.2 mg.

Intended Use: The Nutropin AQ NuSpin 20 is intended to be used by a healthcare professional or patient to deliver Nutropin AQ (somatropin) injection, for subcutaneous use, from an injection device. The device can be used in any setting, including the home, and is disposable.

IMPORTANT NOTES

- Always follow the directions of your healthcare professional and the instructions provided on the back. Contact your healthcare professional if you have any questions.
- Check the label on the NuSpin 20 to make sure the medicine matches your prescription and it has not expired.
- Inspect the cartridge before use to ensure that the medicine in it is clear. If it is cloudy or hazy, do not inject. Return the NuSpin 20 to your healthcare professional.
- Store your NuSpin 20 inside the refrigerator at 2–8°C (36–46°F). Protect from light.

- The product can be used for 28 days after it has been primed and kept under proper storage conditions.
- For the first use of each NuSpin 20, always follow the New NuSpin 20 Set Up Instructions to ensure that air is expelled from the cartridge.
- Do not store with the needle attached. The needle should be removed and safely disposed of immediately after use.
- Keep NuSpin and all medicines out of the reach of young children.

FREQUENTLY ASKED QUESTIONS

1. What type of needles should be used?
  Your Healthcare Professional will recommend a needle that is appropriate for you. The following needles will fit and work on the Nutropin AQ NuSpin:
  - BD Ultra-Fine™ 29 g × 1/2 inch (12.7 mm)
  - BD Ultra-Fine™ Ill short pen needle 31 g × 5/16 inch (8 mm)
  - NovoFine® Autocover® 30 g (8 mm)
  Pen needles from other countries may not fit on your NuSpin device. If you travel outside the United States, make sure you take enough needles for the duration of your stay.
2. Do I need to change the needle every time I use my Nutropin AQ NuSpin?
  Yes. A new needle must be used for every injection. The needle is sterile only for one single injection.
3. Do I need to prime the Nutropin AQ NuSpin each time?
  No. The NuSpin 20 only needs to be primed once, at first use. After the first use of each NuSpin 20, follow the instructions and skip Step 2.
4. When and how do I dispose of my Nutropin AQ NuSpin?
  Your NuSpin 20 is prefilled and the cartridge cannot be replaced. When your NuSpin 20 is empty, dispose of the entire NuSpin 20 as instructed by your healthcare professional. If the empty NuSpin 20 is disposed of with the needle attached, discard the entire device using the same procedure as for needle disposal.

5. Where should I store my Nutropin AQ NuSpin?
  When not in use, your NuSpin 20 should be stored inside a refrigerator at 2–8°C (36–46°F) to maintain the potency of Nutropin AQ (somatropin) injection, for subcutaneous use. During use, we recommend that you have your NuSpin 20 outside of the refrigerator for no longer than one hour per day. When traveling, place your NuSpin 20 in a water-resistant container before placing in a cooler.
  DO NOT FREEZE. KEEP DRY.
6. What should I do if my Nutropin AQ NuSpin is dropped or damaged?
  If you drop the NuSpin 20, check to see if it is damaged. You should also check to see that the black dose knob and the Activator are moving properly. If you notice the NuSpin 20 is damaged, contact your healthcare professional or call 1-866-NUTROPIN for advice.
7. What should I do if my Nutropin AQ NuSpin needs cleaning?
  Use a damp cloth to wipe away dirt. Do not place underwater. Do not use alcohol.

Genentech, Inc., A Member of the Roche Group
1 DNA Way, South San Francisco, CA 94080-4990
Initial US Approval January 2008
NuSpin® is a registered trademark of Genentech, Inc.
Copyright © 2016 Genentech, Inc.

INSTRUCTIONS FOR USE
NEW NuSpin 20 SET UP: STEP-BY-STEP INSTRUCTIONS FOR THE FIRST USE OF EACH NEW NUTROPIN AQ NuSpin 20
STEP 1: Attach the needle |  | STEP 2: Prime the Nutropin AQ NuSpin
Before you begin, wash your hands. Twist gently and pull to remove the NuSpin 20 cap. Inspect the cartridge before use to ensure that the medicine in it is clear. If it is cloudy or hazy, do not inject. Open a new needle by peeling off the paper tab from the needle package. | Attach the needle by carefully screwing the needle onto the needle holder. Do not overtighten. Remove both protective covers from the needle and save the outer cover. | Turn the dose knob to the ℗ position in the dose window. It may take multiple clicks to get to ℗. Hold the NuSpin 20 with the needle pointing upwards. Gently tap the cartridge holder to move any air bubbles to the NuSpin 20 tip. | Slide the Activator toward the needle. If you do not see fluid at the needle tip, redial to and slide the Activator forward again. Repeat until you see fluid.

ROUTINE USE: DOSING AND ADMINISTRATION
STEP 3: Set the dose |  | STEP 4: Give the injection |  | Check dose given
Make sure the dose window reads . Turn the dose knob until the dose prescribed by your healthcare professional appears in the dose window. | If your dose is "between" two numbers in the dose window, the between those two numbers indicates your dose. Turn the dose knob to . The ℗ position indicates a 1.4 mg dose on your NuSpin 20. If you turn the dose knob too far, simply turn it back to the correct dose. (Example above shows a dose of 0.2 mg, represented by). | Select and prepare your injection site as instructed by your healthcare professional. Position your hand so you can easily slide the Activator. Push the needle into the skin. | Slide the Activator toward the needle. Hold the Activator down until the dose knob returns to and continue to hold in place for 5 seconds. Withdraw the Nutropin AQ NuSpin 20 until the needle is removed from the skin. If the dose knob returns to , you have received your full dose. | If the dose knob stops before it returns to , your Nutropin AQ NuSpin 20 is empty and you have not received your full dose. The number shown in the dose window is the amount needed to obtain a full dose. Your healthcare professional will advise you on the procedure for using the last dose in the NuSpin 20.
REMOVAL AND DISPOSAL OF THE NEEDLE
Carefully place the outer cover of the needle package over the needle, unscrew, and dispose of it as instructed by your healthcare professional.
STORAGE AND NEXT USE
Replace the cap and store your NuSpin 20 inside the refrigerator at 2–8°C (36–46°F). Protect from light. For the next use, it is already primed. Follow the instructions and skip Step 2.
Genentech

PRINCIPAL DISPLAY PANEL - 5 mg NuSpin Carton

5 mg

Nutropin AQ® NuSpin® 5

(somatropin) injection, for subcutaneous use
5 mg/2 mL (2.5 mg/mL)

NDC 50242-075-01

Contents: One Nutropin AQ® NuSpin® 5, Instructions for Use, and Package Insert. Each Nutropin AQ® NuSpin® 5 contains 5 mg
(approximately 15 IU) of Nutropin AQ® (somatropin) injection, for subcutaneous use, formulated in 17.4 mg sodium chloride, 5 mg
phenol, 4 mg polysorbate 20, and 10 mM sodium citrate in 2 mL (2.5 mg/mL).
Usage and Administration: For subcutaneous use. Your healthcare professional will recommend a needle that is appropriate
for you (needles not included). See enclosed Package Insert and Instructions for Use.
Storage: Refrigerate at 2–8°C (36–46°F). DO NOT FREEZE. PROTECT FROM LIGHT.

Rx only

KEEP REFRIGERATED

Genentech

10181028

PRINCIPAL DISPLAY PANEL - 10 mg NuSpin Carton

10 mg

Nutropin AQ® NuSpin® 10

(somatropin) injection, for subcutaneous use
10 mg/2 mL (5 mg/mL)

NDC 50242-074-01

Contents: One Nutropin AQ® NuSpin® 10, Instructions for Use, and Package Insert. Each Nutropin AQ® NuSpin® 10 contains 10 mg
(approximately 30 IU) of Nutropin AQ® (somatropin) injection, for subcutaneous use, formulated in 17.4 mg sodium chloride, 5 mg
phenol, 4 mg polysorbate 20, and 10 mM sodium citrate in 2 mL (5 mg/mL).
Usage and Administration: For subcutaneous use. Your healthcare professional will recommend a needle that is appropriate
for you (needles not included). See enclosed Package Insert and Instructions for Use.
Storage: Refrigerate at 2–8°C (36–46°F). DO NOT FREEZE. PROTECT FROM LIGHT.

Rx only

KEEP REFRIGERATED

Genentech

10181029

PRINCIPAL DISPLAY PANEL - 20 mg NuSpin Carton

20 mg

Nutropin AQ® NuSpin® 20

(somatropin) injection, for subcutaneous use
20 mg/2 mL (10 mg/mL)

NDC 50242-076-01

Contents: One Nutropin AQ® NuSpin® 20, Instructions for Use, and Package Insert. Each Nutropin AQ® NuSpin® 20 contains 20 mg
(approximately 60 IU) of Nutropin AQ® (somatropin) injection, for subcutaneous use, formulated in 17.4 mg sodium chloride, 5 mg
phenol, 4 mg polysorbate 20, and 10 mM sodium citrate in 2 mL (10 mg/mL).
Usage and Administration: For subcutaneous use. Your healthcare professional will recommend a needle that is appropriate
for you (needles not included). See enclosed Package Insert and Instructions for Use.
Storage: Refrigerate at 2–8°C (36–46°F). DO NOT FREEZE. PROTECT FROM LIGHT.

Rx only

KEEP REFRIGERATED

Genentech

10181030